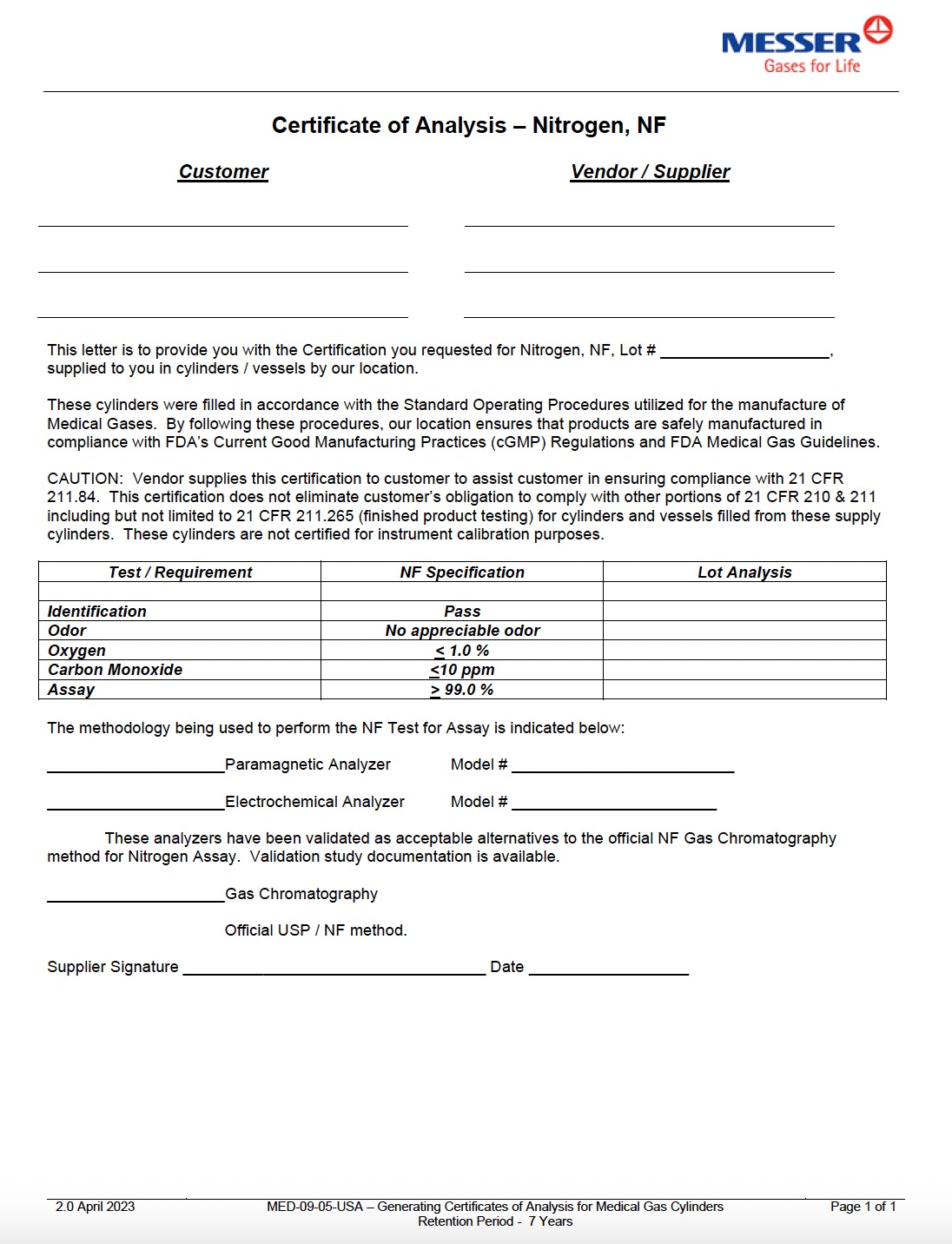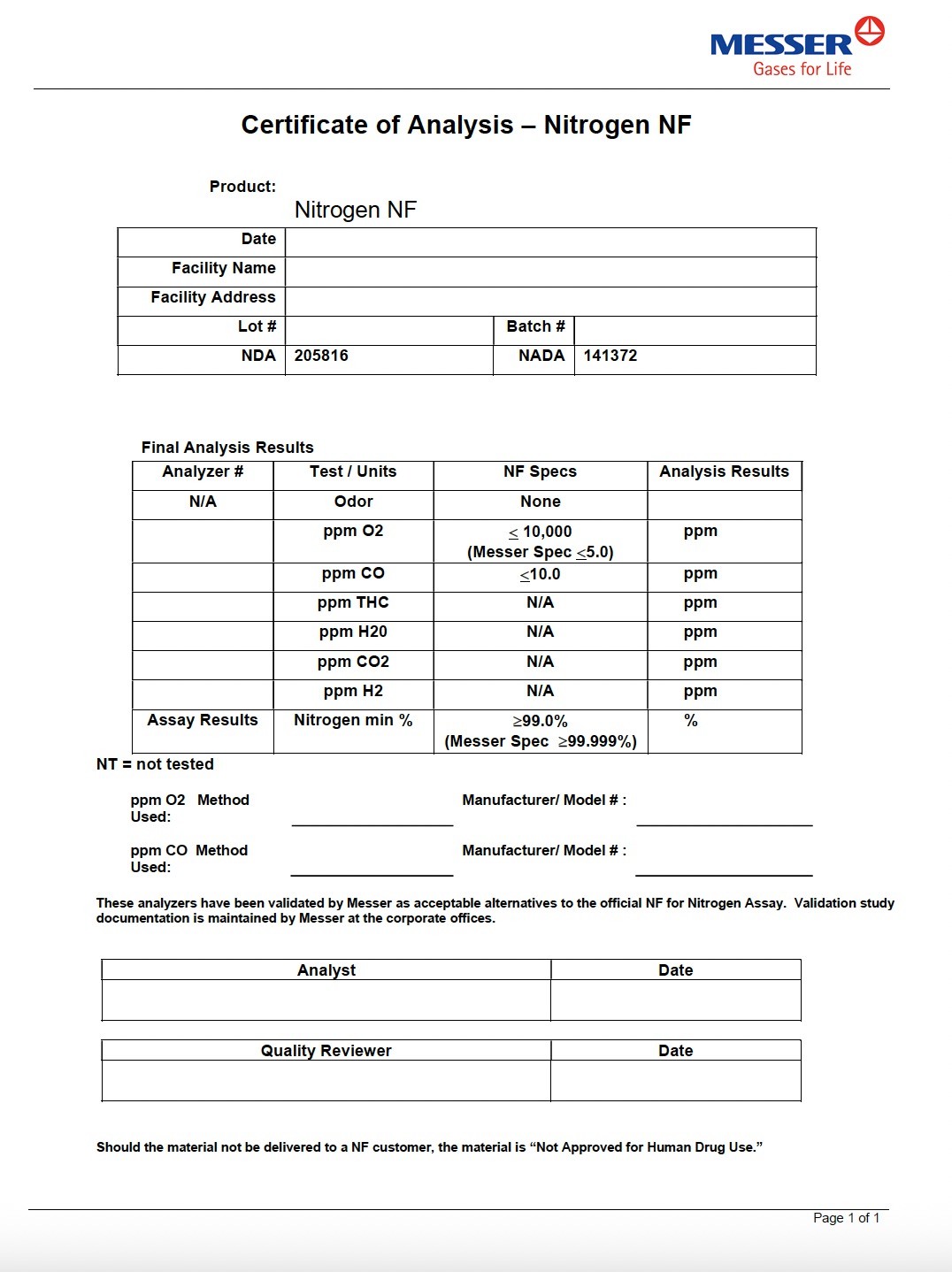 DRUG LABEL: Nitrogen
NDC: 52374-916 | Form: GAS
Manufacturer: Messer Gas Puerto Rico, Inc
Category: animal | Type: PRESCRIPTION ANIMAL DRUG LABEL
Date: 20251209

ACTIVE INGREDIENTS: NITROGEN 995 mL/1 L

PACKAGE LABEL

Certificate of Analysis – Nitrogen, NF

Customer Vendor / Supplier
This letter is to provide you with the Certification you requested for Nitrogen, NF, Lot #.
supplied to you in cylinders / vessels by our location.

These cylinders were filled in accordance with the Standard Operating Procedures utilized for the manufacture of
Medical Gases. By following these procedures, our location ensures that products are safely manufactured in
compliance with FDA’s Current Good Manufacturing Practices (cGMP) Regulations and FDA Medical Gas Guidelines.

CAUTION: Vendor supplies this certification to customer to assist customer in ensuring compliance with 21 CFR
211.84. This certification does not eliminate customer’s obligation to comply with other portions of 21 CFR 210 & 211
including but not limited to 21 CFR 211.265 (finished product testing) for cylinders and vessels filled from these supply
cylinders. These cylinders are not certified for instrument calibration purposes.

Test / Requirement

NF Specification

Lot Analysis

Identification

Pass

Odor

No appreciable odor

Oxygen

< 1.0 %

Carbon Monoxide

≤10 ppm

Assay

≥ 99.0 %

The methodology being used to perform the NF Test for Assay is indicated below:

Paramagnetic Analyzer Model #

Electrochemical Analyzer Model #

These analyzers have been validated as acceptable alternatives to the official NF Gas Chromatography
method for Nitrogen Assay. Validation study documentation is available.

Gas Chromatography

Official USP / NF method.

Supplier Signature Date

PACKAGE LABEL

Certificate of Analysis – Nitrogen NF

Product:
Nitrogen NF

Date

Facility Name

Facility Address

Lot #

NDA

205816

Batch #

NADA 141372

Final Analysis Results

Analyzer #

Test / Units

NF Specs

Analysis Results

N/A

Odor

None

ppm O₂

≤ 10,000

ppm

(Messer Spec ≤5.0)

ppm CO

≤10.0

ppm

ppm THC

N/A

ppm

ppm H₂O

N/A

ppm

ppm CO₂

N/A

ppm

ppm H₂

N/A

ppm

Assay Results

Nitrogen min %

≥99.0%

%

(Messer Spec ≥99.999%)

NT = not tested

ppm O₂ Method Used: Manufacturer / Model #:

ppm CO Method Used: Manufacturer / Model #:

These analyzers have been validated by Messer as acceptable alternatives to the official NF for Nitrogen Assay.
Validation study documentation is maintained by Messer at the corporate offices.

Analyst

Date

Quality Reviewer

Date

Should the material not be delivered to a NF customer, the material is “Not Approved for Human Drug Use.”